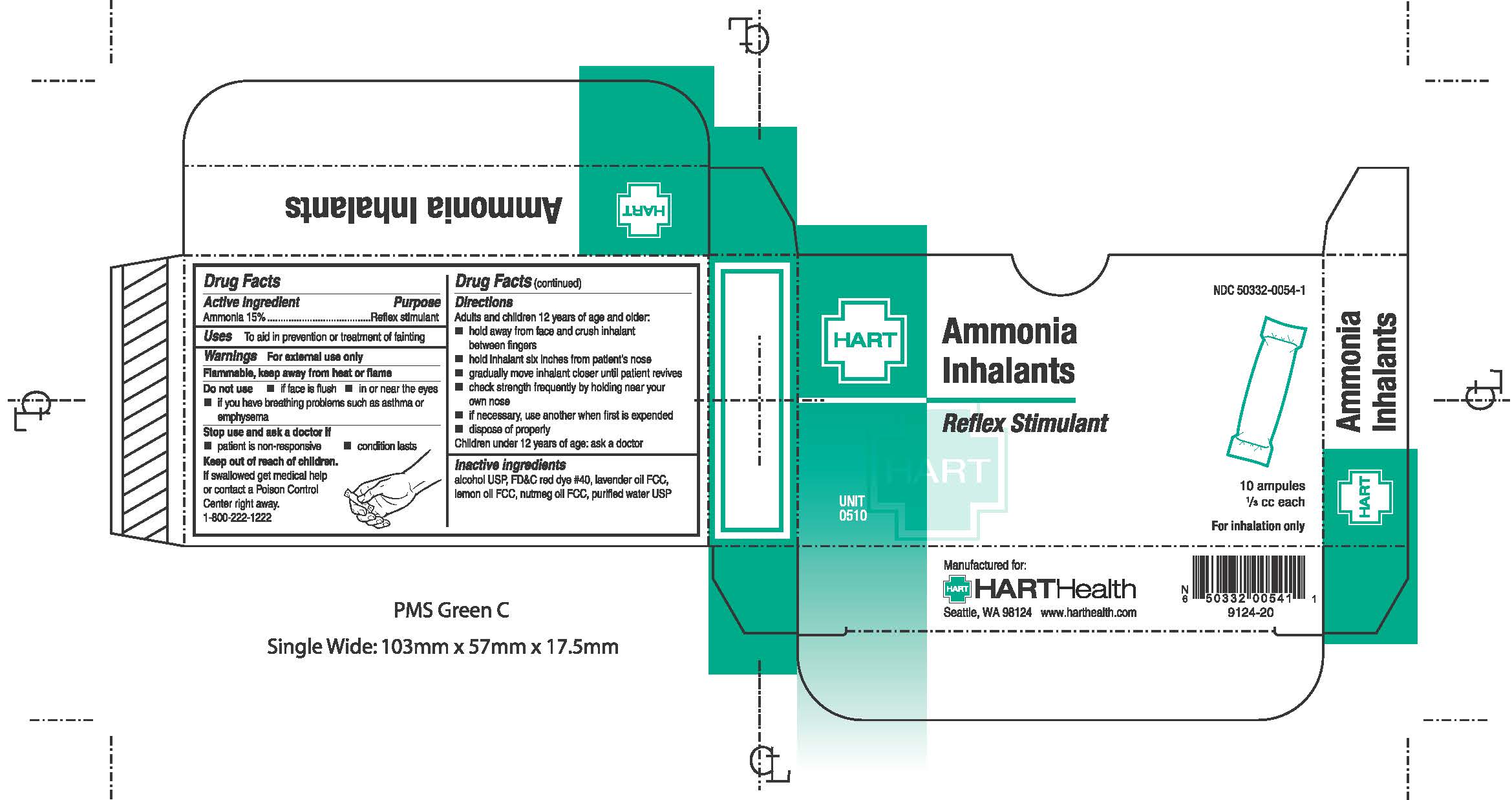 DRUG LABEL: Ammonia Inhalants
NDC: 50332-0054 | Form: INHALANT
Manufacturer: HART Health
Category: otc | Type: HUMAN OTC DRUG LABEL
Date: 20210104

ACTIVE INGREDIENTS: AMMONIA 0.15 g/1 g
INACTIVE INGREDIENTS: ALCOHOL; FD&C RED NO. 40; WATER

Active Ingredient: Ammonia 15%

Purpose:

Reflex Stimulant

Uses:

to aid in prevention and treatment of fainting

Warnings:

For external use only

Flammable, keep away from heat or flame

Do not use:

- if face is flush
- in or near the eyes
- if you have breathing problems such as asthma or emphysema

Stop use and ask a doctor if:

- patient is non-responsive
- condition lasts

Keep out of reach of children.

If swallowed get medical help or contact a Poison Control Center right away. 1-800-1222

DOSAGE AND ADMINISTRATION

Adults and children 12 years of age and older:

- hold away from face and crush inhalant between fingers
- hold packet six inches from patient's nose
- gradually move inhalant closer until patient revives
- check strength frequently by holding near your own nose
- if necessary, use another when first is expended
- dispose of properly

Children under 12 years of age: ask a doctor

INACTIVE INGREDIENT

Inactive ingredients: alcohol USP, FD&C red dye #40, lavender oil FCC, lemon oil FCC, nutmeg oil FCC, purified water USP